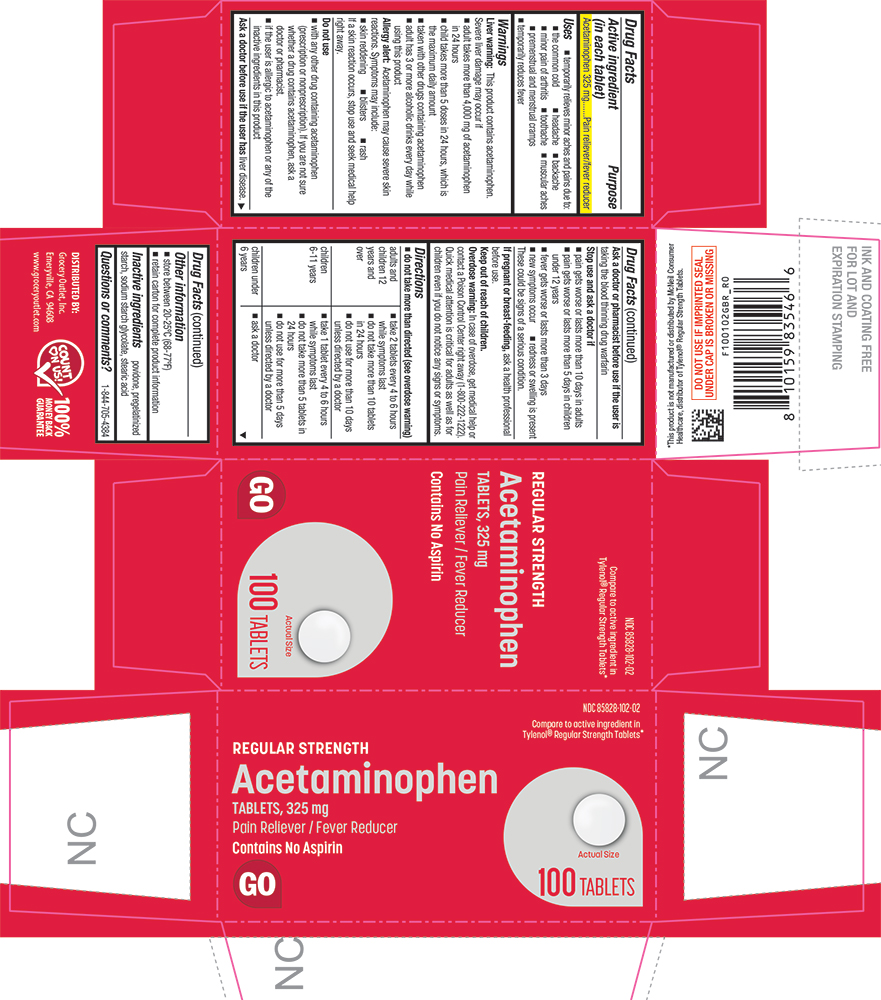 DRUG LABEL: Acetaminophen
NDC: 85828-102 | Form: TABLET
Manufacturer: Grocery Outlet, Inc.
Category: otc | Type: HUMAN OTC DRUG LABEL
Date: 20260218

ACTIVE INGREDIENTS: ACETAMINOPHEN 325 mg/1 1
INACTIVE INGREDIENTS: POVIDONE, UNSPECIFIED; STARCH, PREGELATINIZED CORN; SODIUM STARCH GLYCOLATE TYPE A CORN; STEARIC ACID

1001-GBR-2026-0218

Drug Facts

Active ingredient (in each tablet)

Acetaminophen 325 mg

Purpose

Pain reliever/fever reducer

Uses

- temporarily relieves minor aches and pains due to:
  - the common cold
  - headache
  - backache
  - minor pain of arthritis
  - toothache
  - muscular aches
  - premenstrual and menstrual cramps
- temporarily reduces fever

Warnings

Liver warning

This product contains acetaminophen. Severe liver damage may occur if

- adult takes more than 4,000 mg of acetaminophen in 24 hours
- child takes more than 5 doses in 24 hours, which is the maximum daily amount
- taken with other drugs containing acetaminophen
- adult has 3 or more alcoholic drinks every day while using this product

Allergy alert

acetaminophen may cause severe skin reactions. Symptoms may include:

- skin reddening
- blisters
- rash

If a skin reaction occurs, stop use and seek medical help right away.

Do not use

- with any other drug containing acetaminophen (prescription or nonprescription). If you are not sure whether a drug contains acetaminophen, ask a doctor or pharmacist.
- if the user is allergic to acetaminophen or any of the inactive ingredients in this product

Ask a doctor before use if the user hasliver disease.

Ask a doctor or pharmacist before use if the user istaking the blood thinning drug warfarin

Stop use and ask a doctor if

- pain gets worse or lasts more than 10 days in adults
- pain gets worse or lasts more than 5 days in children under 12 years
- fever gets worse or lasts more than 3 days
- new symptoms occur
- redness or swelling is present

These could be signs of a serious condition.

PREGNANCY OR BREAST FEEDING

If pregnant or breast-feeding,ask a health professional before use.

Overdose warning

In case of overdose, get medical help or contact a Poison Control Center right away (1-800-222-1222). Quick medical attention is critical for adults as well as for children even if you do not notice any signs or symptoms.

Directions

- do not take more than directed (see overdose warning)

adults and children 12 years and over | - take 2 tablets every 4 to 6 hours while symptoms last - do not take more than 10 tablets in 24 hours - do not use for more than 10 days unless directed by a doctor
children 6-11 years | - take 1 tablet every 4 to 6 hours while symptoms last - do not take more than 5 tablets in 24 hours - do not use for more than 5 days unless directed by a doctor
children under 6 years | - ask a doctor

Other information

- store between 20-25°C (68-77°F)
- retain carton for complete product information

Inactive ingredients

povidone, pregelatinized starch, sodium starch glycolate, stearic acid

Questions or comments?

1-844-705-4384

PRINCIPAL DISPLAY PANEL

NDC 85828-102-02

Compare to the active ingredient in Tylenol® Regular Strength Tablets*

REGULAR STRENGTH

Acetaminophen

TABLETS, 325 mg

Pain Reliever / Fever Reducer

Contains No Aspirin

GO

Actual Size

100 TABLETS